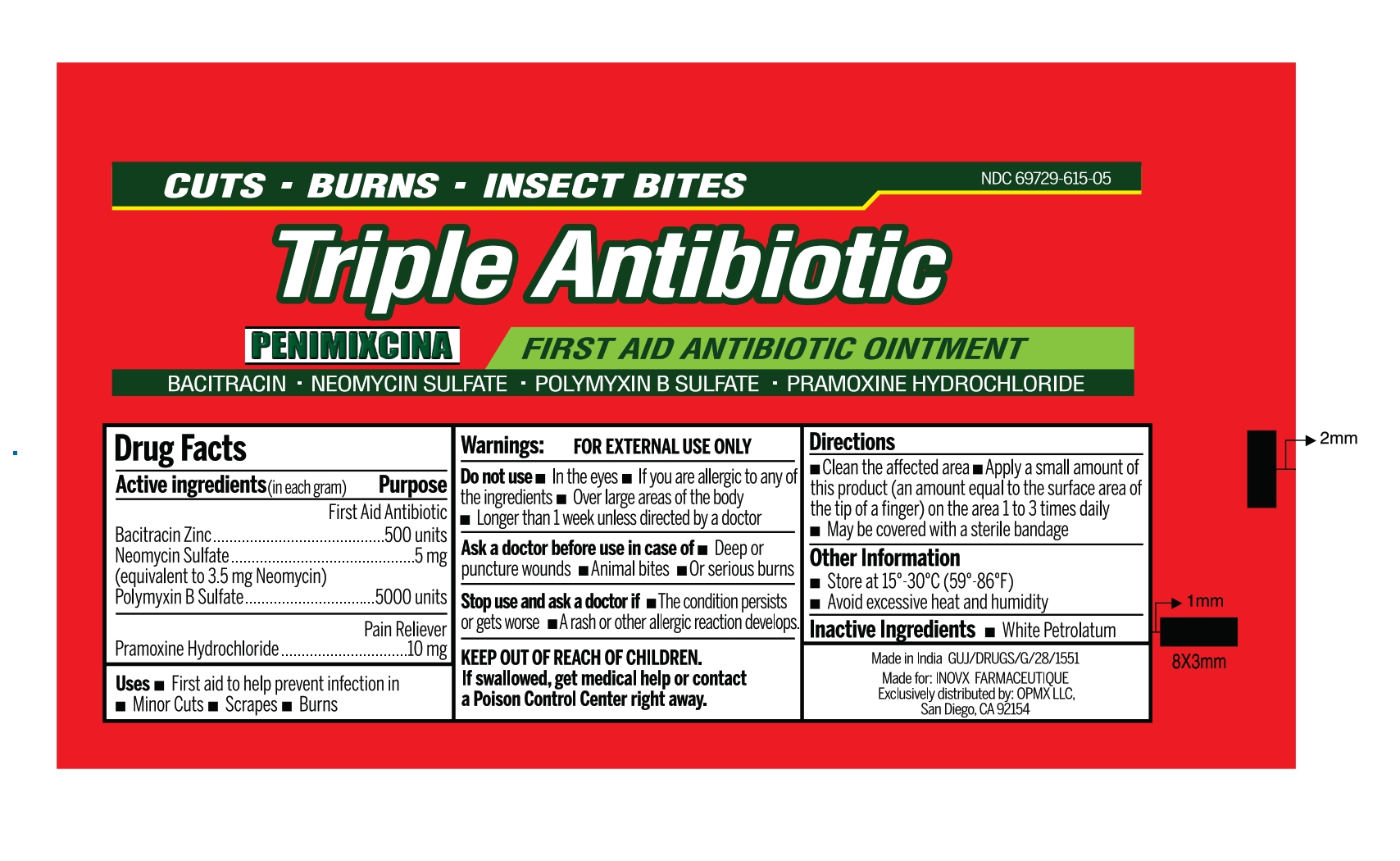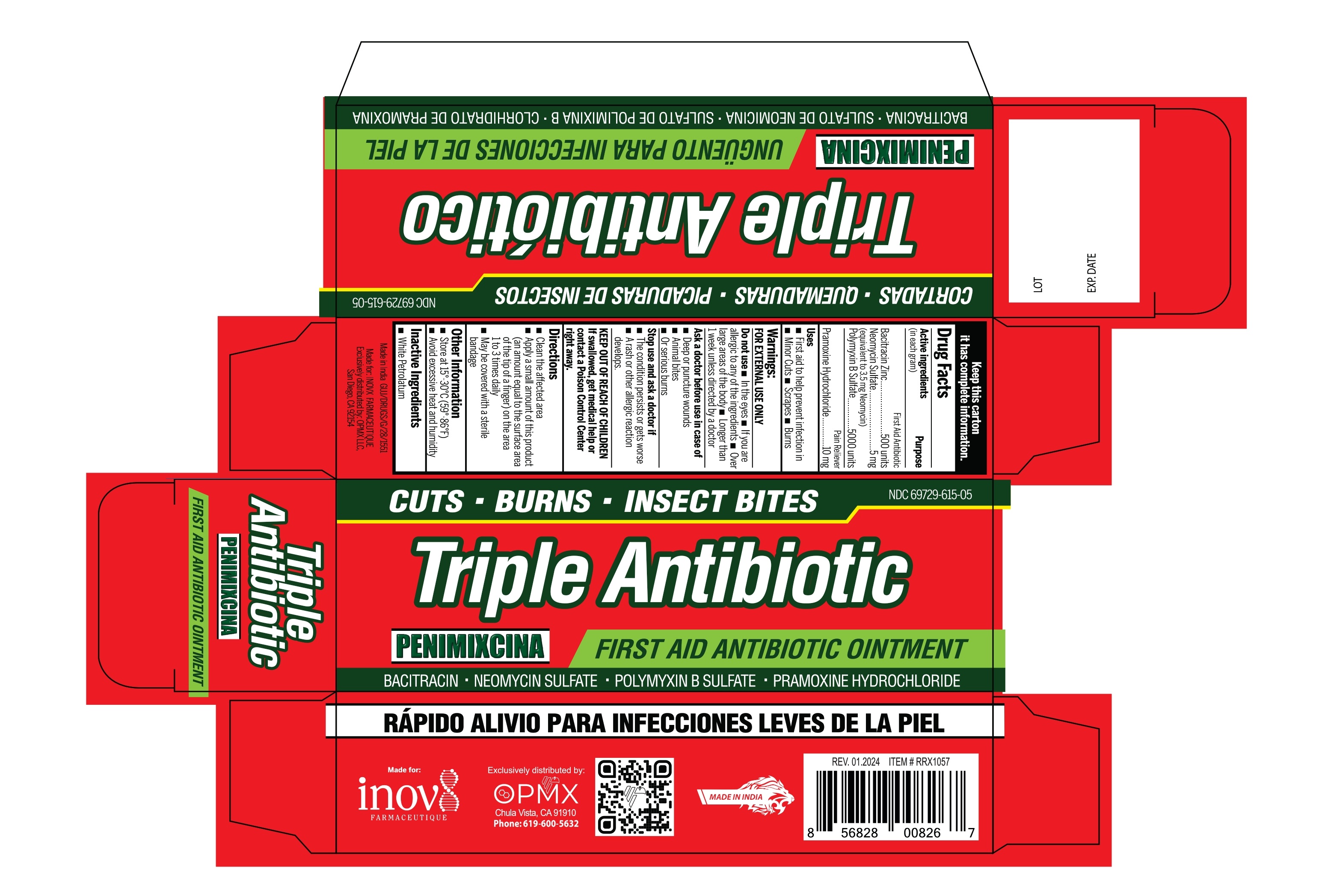 DRUG LABEL: PENIMIXCINA
NDC: 69729-615 | Form: OINTMENT
Manufacturer: OPMX LLC
Category: otc | Type: HUMAN OTC DRUG LABEL
Date: 20240517

ACTIVE INGREDIENTS: BACITRACIN ZINC 500 [iU]/1 g; NEOMYCIN SULFATE 5 mg/1 g; POLYMYXIN B SULFATE 5000 [iU]/1 g; PRAMOXINE HYDROCHLORIDE 10 mg/1 g
INACTIVE INGREDIENTS: PETROLATUM

Penimixcina - First Aid Ointment

ACTIVE INGREDIENTS (IN EACH GRAM)

BACITRACIN ZINC 500 UNITS

NEOMYCIN SULFATE 5 MG (EQUIVALENT TO 3.5 MG NEOMYCIN)

POLYMYXIN B SULFATE 5000 UNITS

PRAMOXINE HYCHLORIDE 10 MG

PURPOSE

FIRST AID ANTIBIOTIC

PAIN RELIEVER

USES

- FIRST AID TO HELP PREVENT INFECTION IN
- MINOR CUTS
- SCRAPES
- BURNS

WARNINGS

For external use only.

DO NOT USE

- IN THE EYES
- IF YOU ARE ALLERGIC TO ANY OF THE INGREDIENTS
- OVER LARGE AREAS OF THE BODY
- LONGER THAN 1 WEEK UNLESS DIRECTED BY A DOCTOR

ASK A DOCTOR BEFORE USE IN CASE OF

- DEEP OR PUNCTURE WOUNDS
- ANIMAL BITES
- OR SERIOUS BURNS

STOP USE AND ASK A DOCTOR IF

- The condition persists or gets worse
- A rash or other allergic reaction develops

Keep out of reach of children

- If swallowed get medical help or contact Poison Control Center right away.

DIRECTIONS

- CLEAN THE AFFECTED AREA
- APPLY A SMALL AMOUNT OF THIS PRODUCT (AN AMOUNT EQUAL TO THE SURFACE AREA OF THE TIP OF A FINGER) ON THE AREA 1 TO 3 TIMES DAILY
- MAY BE COVERED WITH A STERILE BANDAGE

INACTIVE INGREDIENTS

WHITE PETROLATUM

OTHER INFORMATION

- STORE AT 15° - 30°C (59°F - 86°F)
- AVOID EXCESSIVE HEAT AND HUMIDITY

Penimixcina First Aid Ointment

NDC 69729-615-05